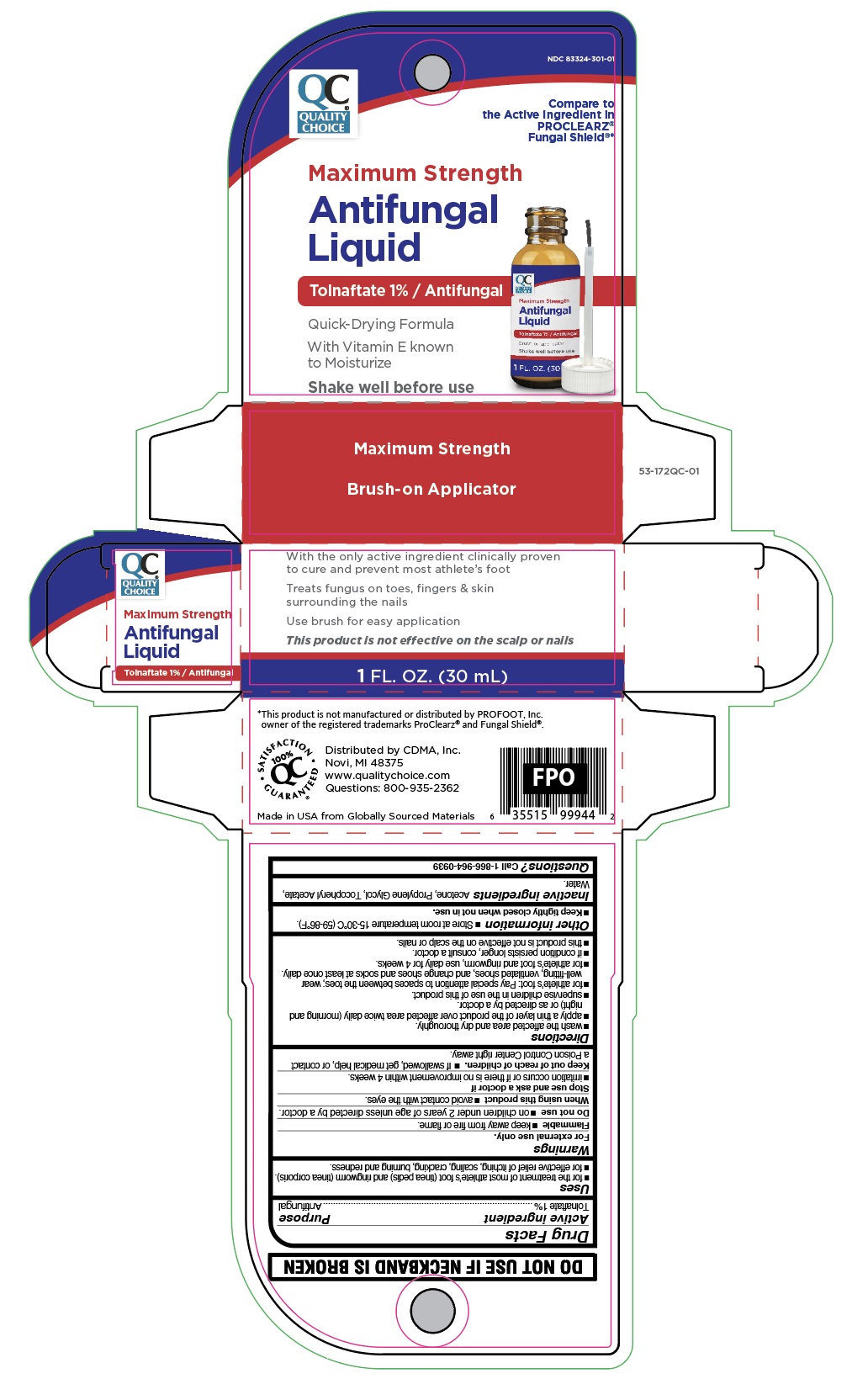 DRUG LABEL: Maximum Strength Antifungal Liquid
NDC: 83324-301 | Form: LIQUID
Manufacturer: Chain Drug Marketing Association Inc
Category: otc | Type: HUMAN OTC DRUG LABEL
Date: 20251106

ACTIVE INGREDIENTS: TOLNAFTATE 10 mg/1 mL
INACTIVE INGREDIENTS: WATER; TOCOPHEROL; ACETONE; PROPYLENE GLYCOL

Quality Choice Maximum Strength Antifungal Liquid

Active ingredient

Tolnaftate 1%

Purpose

Antifungal

Uses

- For the treament of athlete's foot (tinea pedis) and ring worm (tinea corporis).
- For effective relief of itching, scaling, cracking, burning, and redness.

Warnings

For external use only.

Flammable

- Keep away from fire or flame.

Do not use

on children under 2 years of age unless directed by a doctor.

When using this product

avoid contact with the eyes.

Stop use and consult a doctor if

- irritation occurs or if there is no improvement within 4 weeks.

Keep out of reach of children.

If swallowed, get medical help or contact a Poison Control Center right away.

Directions

- wash the affected area and dry thoroughly.
- apply a thin layer of the product over the affected area twice daily (morning and night) or as directed by a doctor.
- supervise children in the use of this product.
- for athlete's foot: pay special attention to spaces between toes; wear well-fitting, ventilated shoes, and change shoes and socks at least once daily.
- for athlete's foot and ringworm, use daily for 4 weeks.
- If condition persists longer, consult a doctor.
- this product is not effective on the scalp or nails.

Other information

- store at room temperature 15°-30°C (59° - 86°F).
- keep tightly closed when not in use.

Inactive ingredient

Acetone, Propylene Glycol, Tocopherol Acetate, Water.

Questions?

Call 1-866-964-0939

Principal Display Panel

QC

Quality

Choice

Maximum Strength

Antifungal

Liquid

Tolnaftate 1% / Antifungal

Quick-Drying Formula

With Vitamin E known

to Moisturize

Shake well before use

With the only active ingredient clinically proven

to cure and prevent most athlete's foot

Treats fungus on toes, fingers & skin

surrounding the nails

Use brush for easy application

This product is not effective on the scalp or nails

1 FL. OZ. (30 mL)